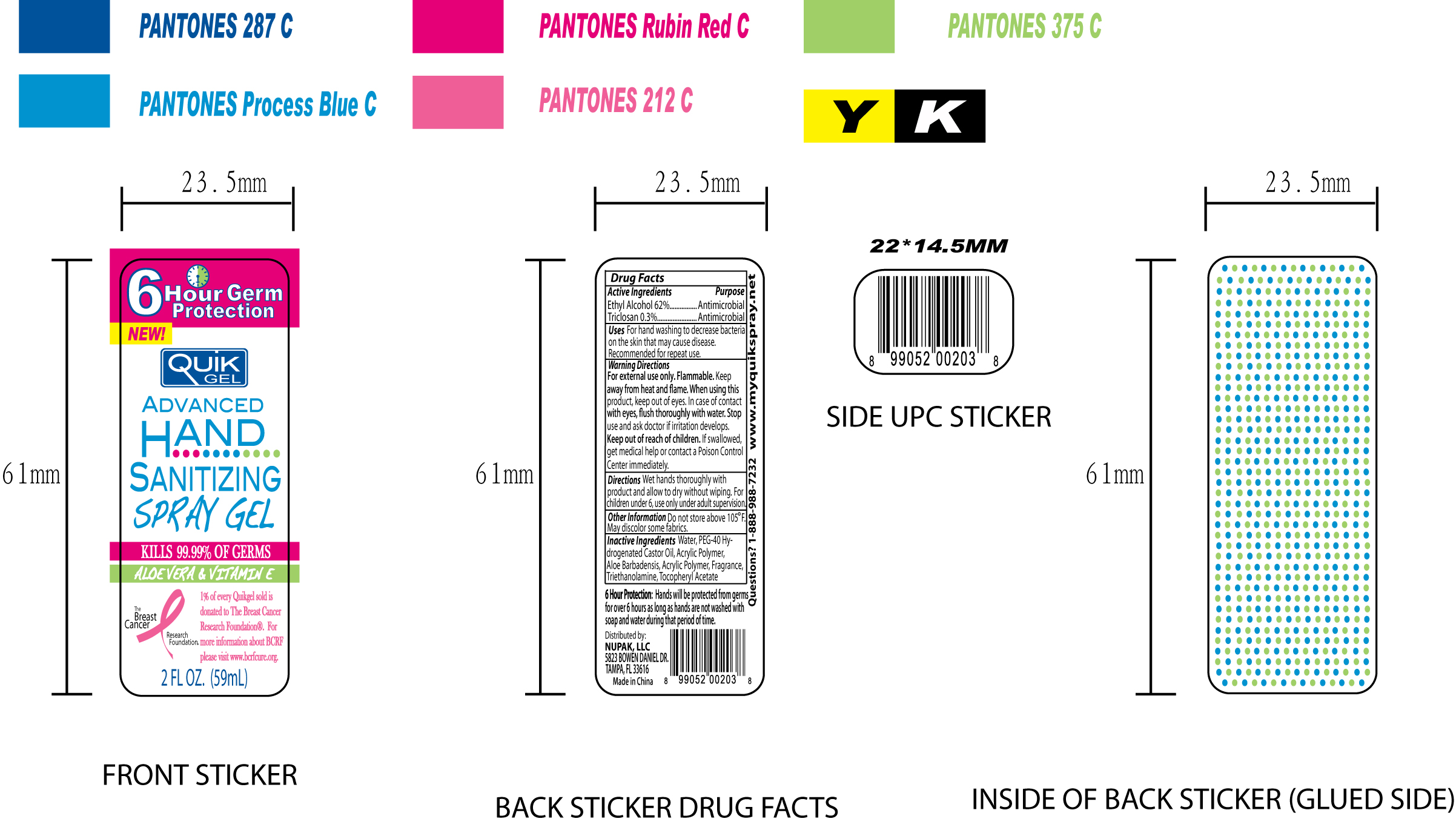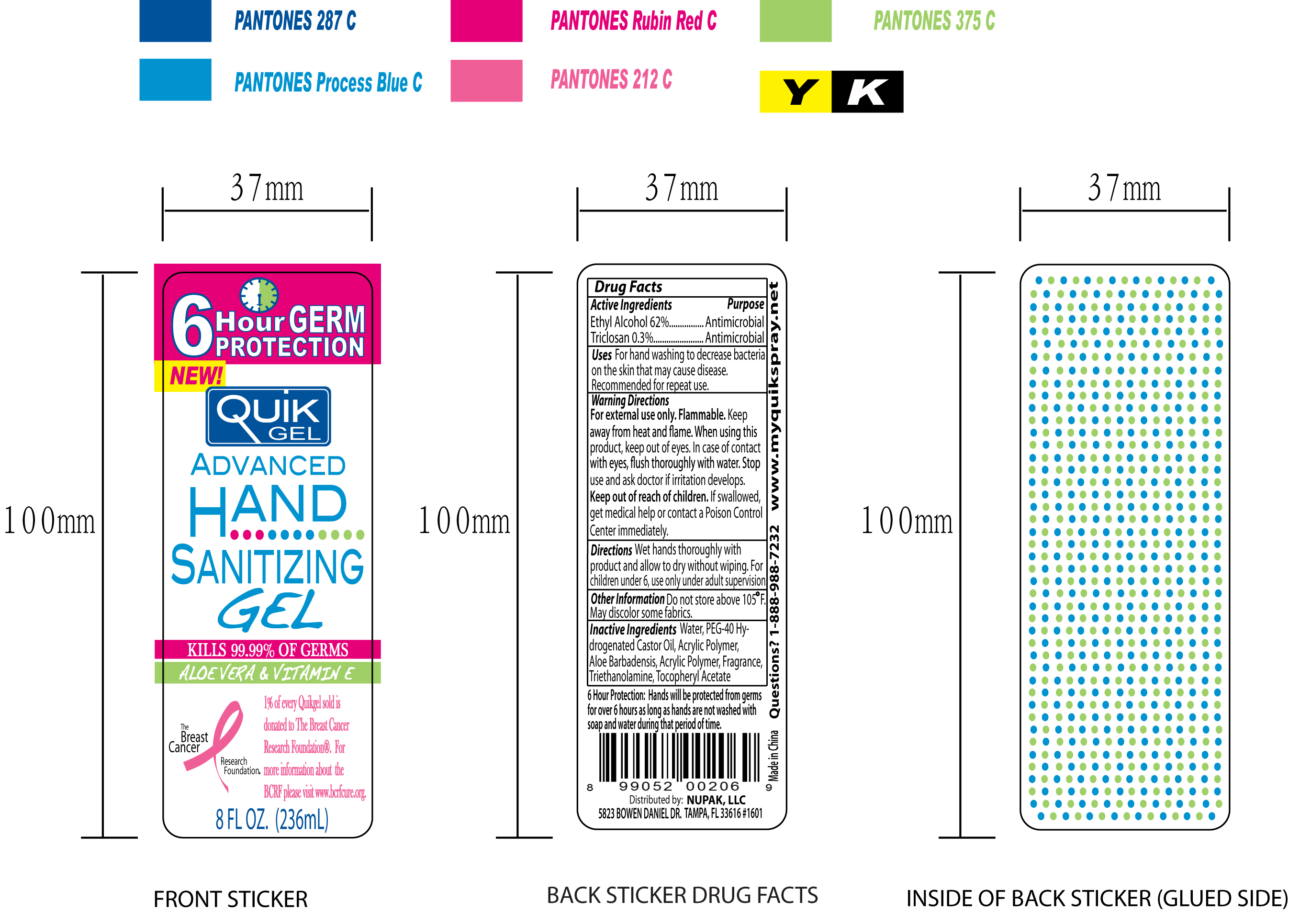 DRUG LABEL: Quik Gel
NDC: 41900-100 | Form: GEL
Manufacturer: Cinogen Cosmetics Zhaoqing, LTD.
Category: otc | Type: HUMAN OTC DRUG LABEL
Date: 20090903

ACTIVE INGREDIENTS: ALCOHOL 0.62 mL/1 mL; TRICLOSAN 0.03 mL/1 mL
INACTIVE INGREDIENTS: WATER; POLYOXYL 40 HYDROGENATED CASTOR OIL; ALOE VERA LEAF; TROLAMINE; ALPHA-TOCOPHEROL ACETATE; CARBOMER HOMOPOLYMER TYPE C

Quik Gel Advanced Hand Sanitizing Gel

Active Ingredients Purpose

Ethyl Alcohol 62 percent Antimicrobial

Triclosan 0.3 percent Antimicrobial

PURPOSE

Uses For hand washing to decrease bacteria on the skin that may cause disease.

Recommended for repeat use.

WARNINGS

Warning Directions

For external use only. Flammable. Keep away from heat and flame. When using this product, keep out of eyes.

In case of contact with eyes, flush thoroughly with water.

Stop use and ask doctor if irritation develops.

Keep out of reach of children. If swallowed, get medical help or contact a Poison Control Center immediately.

Directions

Wet hands thoroughly with product and allow to dry without wiping.

For children under 6, use only under adult supervision.

Other Information

Do not store above 105 degrees F. May discolor some fabrics.

Inactive Ingredients

Water, PEG-40 Hydrogenated Castor Oil, Acrylic Polymer, Aloe Barbadensis, Acrylic Polymer, Fragrance, Triethanolamine, Tocopheryl Acetate

Questions? 1-888-988-7232

www.myquikspray.net

PATIENT COUNSELING INFORMATION

6 Hour Protection: Hands will be protected from germs for over 6 hours as long as hands are not washed with soap and water during that period of time.